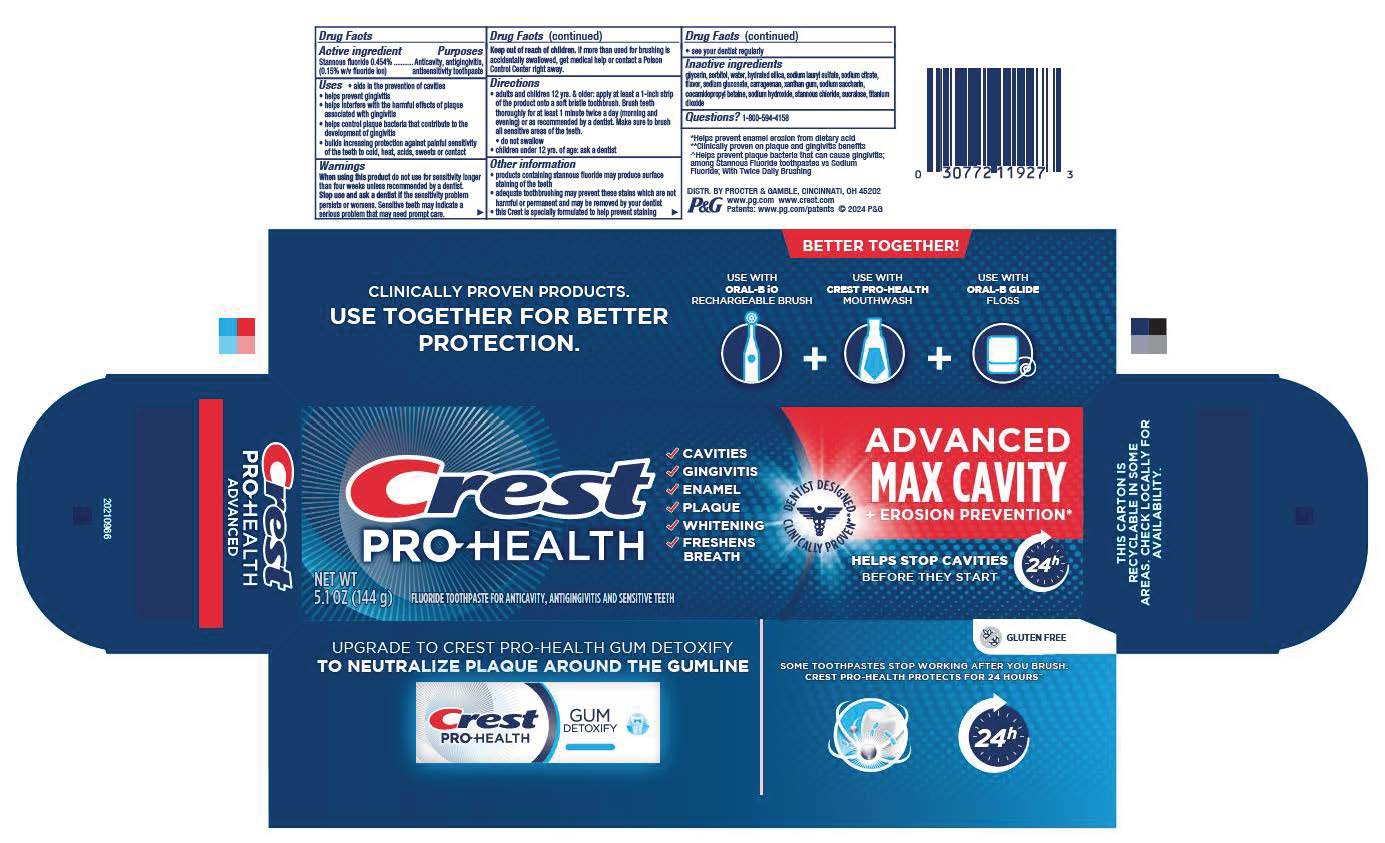 DRUG LABEL: Crest Pro-Health
NDC: 84126-624 | Form: PASTE, DENTIFRICE
Manufacturer: The Procter & Gamble Manufacturing Company
Category: otc | Type: HUMAN OTC DRUG LABEL
Date: 20260121

ACTIVE INGREDIENTS: STANNOUS FLUORIDE 1.5 mg/1 g
INACTIVE INGREDIENTS: SODIUM HYDROXIDE; SACCHARIN SODIUM; XANTHAN GUM; GLYCERIN; SODIUM LAURYL SULFATE; SORBITOL; TITANIUM DIOXIDE; COCAMIDOPROPYL BETAINE; SUCRALOSE; STANNOUS CHLORIDE; SODIUM CITRATE; WATER; HYDRATED SILICA; CARRAGEENAN; SODIUM GLUCONATE

Crest Pro-Health Advanced Max Cavity and Erosion Prevention

Drug Facts

Active ingredient

Stannous fluoride 0.454%

(0.15% w/v fluoride ion)

Purposes

Anticavity, antigingivitis, antisensitivity toothpaste

Uses

- aids in the prevention of cavities
  • helps prevent gingivitis
  • helps interfere with the harmful effects of plaque
  associated with gingivitis
  • helps control plaque bacteria that contribute to the
  development of gingivitis
  • builds increasing protection against painful sensitivity
  of the teeth to cold, heat, acids, sweets or contact

Keep out of reach of children. If more than used for brushing is
accidentally swallowed, get medical help or contact a Poison
Control Center right away.

When using this product do not use for sensitivity longer than four weeks unless recommended by a dentist.

Stop use and ask a dentist if the sensitivity problem persists or worsens. Sensitive teeth may indicate a serious problem that may need prompt care.

Keep out of reach of children. If more than used for brushing is accidentally swallowed, get medical help or contact a Poison Control Center right away.

Directions

- adults and children 12 yrs. & older: apply at least a 1-inch strip
  of the product onto a soft bristle toothbrush. Brush teeth
  thoroughly for at least 1 minute twice a day (morning and
  evening) or as recommended by a dentist. Make sure to brush
  all sensitive areas of the teeth.
  • do not swallow
  • children under 12 yrs. of age: ask a dentist

Other information

- products containing stannous fluoride may produce surface staining of the teeth
- adequate toothbrushing may prevent these stains which are not harmful or permanent and may be removed by your dentist
- this Crest is specially formulated to help prevent staining
- see your dentist regularly

Inactive ingredients

glycerin, sorbitol, water, hydrated silica, sodium lauryl sulfate, sodium citrate, flavor, sodium gluconate, carrageenan, xanthan gum, sodium saccharin, cocamidopropyl betaine, sodium hydroxide, stannous chloride, sucralose, titanium dioxide

Questions?

1-800-594-4158

DISTR. BY PROCTER & GAMBLE,

CINCINNATI, OH 45202

Principal Display Panel - 116 g tube in carton

Crest

Pro-Health

NET WT

5.1 OZ (144 g)

FLUORIDE TOOTHPASTE FOR ANTICAVITY, ANTIGINGIVITIS AND SENSITIVE TEETH

CAVITIES

GINGIVITIS

ENAMEL

PLAQUE

WHITENING

FRESHENS

BREATH

ADVANCED

MAX CAVITY

+ EROSION PREVENTION

DENTIST DESIGNED

CLINICALLY PROVEN

HELPS STOP CAVITIES

BEFORE THEY START

24h